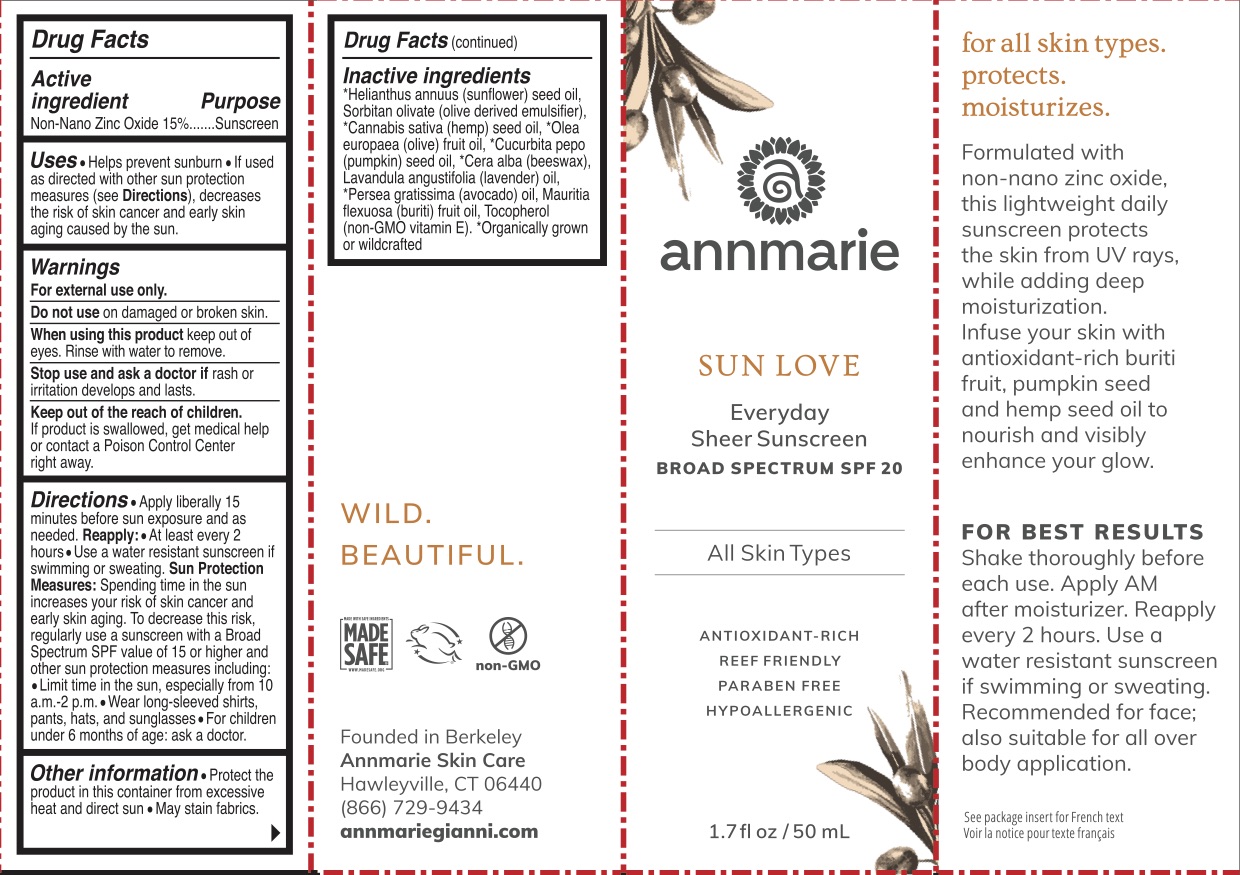 DRUG LABEL: Annmarie SPF 20 Sunscreen
NDC: 82052-157 | Form: LOTION
Manufacturer: Annmarie Gianni Skin Care LLC
Category: otc | Type: HUMAN OTC DRUG LABEL
Date: 20241215

ACTIVE INGREDIENTS: ZINC OXIDE 15 g/100 mL
INACTIVE INGREDIENTS: SUNFLOWER OIL; SORBITAN OLIVATE; CANNABIS SATIVA SEED OIL; OLIVE OIL; PUMPKIN SEED OIL; YELLOW WAX; LAVENDER OIL; AVOCADO OIL; MAURITIA FLEXUOSA FRUIT OIL; TOCOPHEROL

Active Ingredients

Zinc Oxide 15%

Purpose

Sunscreen

Uses

Helps prevent sunburn. If used as directed with other sun protection measures (see Directions) decreases the risk of skin cancer and early skin aging caused by the sun.

Warnings

For external use only.

Do not use on damaged or broken skin. When using this product keep out of eyes. Rinse eyes with water to remove.

Stop use and ask a doctor if rash occurs.

Keep Out of Reach of Children.

If swallowed, get medical help or contact a Poison Control Center right away.

Directions

Apply liberally 15 minutes before sun exposure. Reapply:

- after 80 minutes of swimming or sweating
- immediately after towel drying
- at least every 2 hours
- use a water resistant sunscreen if swimming or sweating

Sun protection measures: spending time in the sun increases your risk of skin cancer and early skin aging. To decrease risk, regularly use a sunscreen with broad spectrum SPF value of 15 or higher and other sun protection measure including:

- limit time in the sun, especially from 10 am to 2 pm
- wear long-sleeved shirts, pants, hats, and sunglasses.
- Children under 6 months: ask a doctor.

Inactive Ingredients

Helianthus Annuus (Sunflower) Seed Oil*, Sorbitan Olivate, Cannabis Sativa Seed Oil*, Olea Europaea (Olive) Fruit Oil*, Cucurbita Pepo (Pumpkin) Seed Oil*, Beeswax*, Lavandula Angustifolia (Lavender) Oil, Persea Gratissima (Avocado) Oil*, Mauritia Flexuosa Fruit Oil, Tocopherol. *Organic